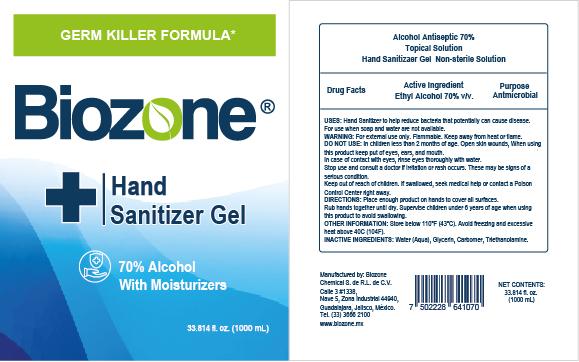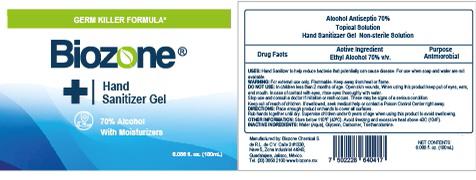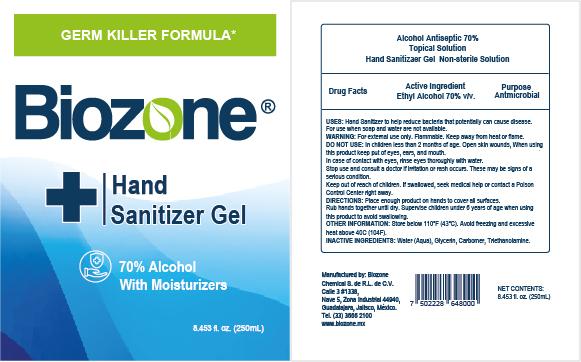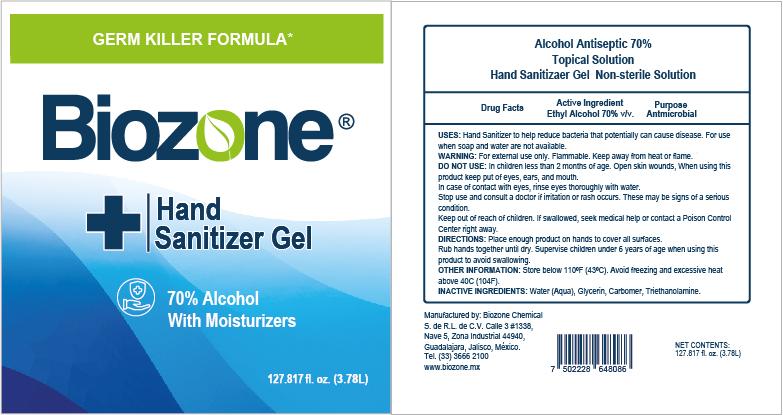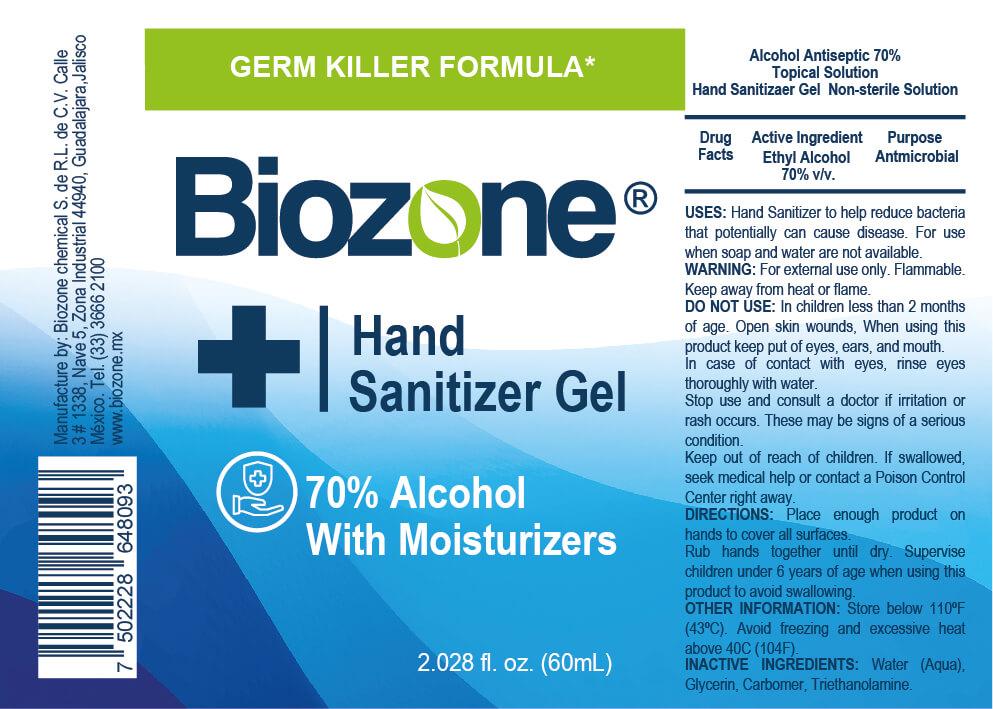 DRUG LABEL: BIOZONE
NDC: 78349-0003 | Form: GEL
Manufacturer: Biozone Chemical, S. de R.L. de C.V.
Category: otc | Type: HUMAN OTC DRUG LABEL
Date: 20210216

ACTIVE INGREDIENTS: ALCOHOL 0.7 mL/1 mL
INACTIVE INGREDIENTS: WATER 0.2585 mL/1 mL; TRIETHANOLAMINE CAPROYL GLUTAMATE 0.002 mL/1 mL; GLYCERIN 0.0375 mL/1 mL; CARBOMER 940 0.002 mL/1 mL

BIOZONE HAND SANITIZER GEL

ACTIVE INGREDIENT SECTION

Active ingredient Ethyl Alcohol 70%

DOSAGE AND ADMINISTRATION SECTION

Place enough product on hands to cover all surfaces. Rub hands together until dry.

INACTIVE INGREDIENT SECTION

Inactive ingredients Water (Aqua), Glycerin, Carbomer, Triethanolamine

INDICATIONS AND USAGE SECTION

When using this product keep out of eyes, ears, and mouth. In case of contact with eyes, rinse eyes thoroughly with water.

Place enough product on hands to cover all surfaces. Rub hands together until dry.

Supervise children under 6 years of age when using this product to avoid swallowing.

Keep out of reach of children. If swallowed, get medical help or contact a Poison Control Center right away.

PURPOSE

Purpose Antmicrobial

WARNINGS

For external use only. Flammable. Keep away from heat or flame

WARNINGS AND PRECAUTIONS

Warnings

For external use only. Flammable. Keep away from heat or flame

When using this product keep out of eyes, ears, and mouth. In case of contact with eyes, rinse eyes thoroughly with water.

ASK A DOCTOR

Stop use and ask a doctor if irritation or rash occurs. These may be signs of a serious condition.